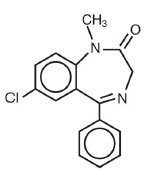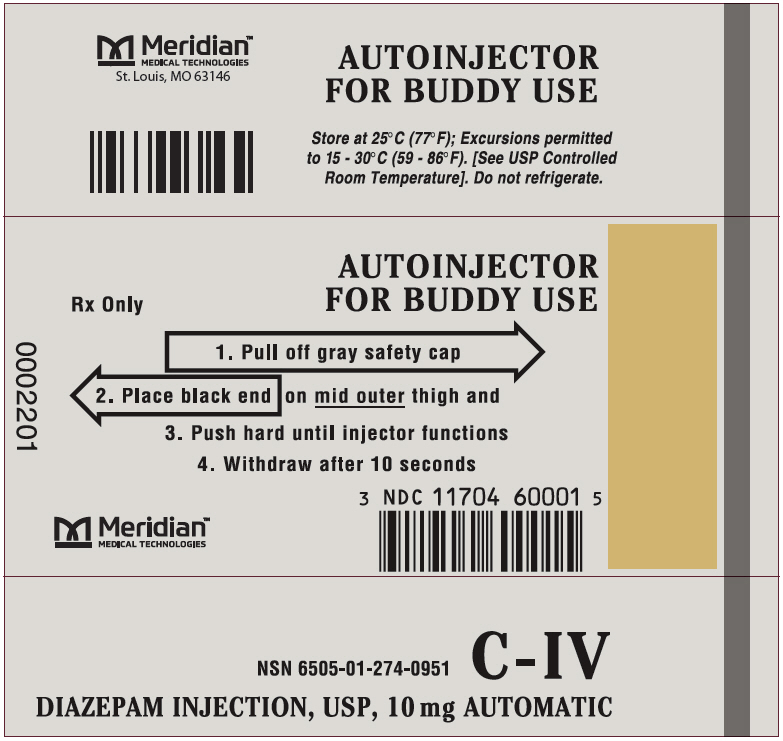 DRUG LABEL: Diazepam
NDC: 11704-600 | Form: INJECTION
Manufacturer: Meridian Medical Technologies LLC
Category: prescription | Type: HUMAN PRESCRIPTION DRUG LABEL
Date: 20231218
DEA Schedule: CIV

ACTIVE INGREDIENTS: diazepam 10 mg/2 mL
INACTIVE INGREDIENTS: Sodium Benzoate; Benzoic Acid; Propylene Glycol; Alcohol; Benzyl Alcohol; Water; Nitrogen; Sodium Hydroxide

DIAZEPAM AUTOINJECTOR C-IV

Rx Only

WARNING: RISKS FROM CONCOMITANT USE WITH OPIOIDS; ABUSE, MISUSE, AND ADDICTION; and DEPENDENCE AND WITHDRAWAL REACTIONS

- Concomitant use of benzodiazepines and opioids may result in profound sedation, respiratory depression, coma, and death. Reserve concomitant prescribing of these drugs for patients for whom alternative treatment options are inadequate. Limit dosages and durations to the minimum required. Follow patients for signs and symptoms of respiratory depression and sedation (see WARNINGS and PRECAUTIONS).
- The use of benzodiazepines, including Diazepam injection, exposes users to risks of abuse, misuse, and addiction, which can lead to overdose or death. Abuse and misuse of benzodiazepines commonly involve concomitant use of other medications, alcohol, and/or illicit substances, which is associated with an increased frequency of serious adverse outcomes. Before prescribing Diazepam injection and throughout treatment, assess each patient's risk for abuse, misuse, and addiction (see WARNINGS).
- The continued use of benzodiazepines may lead to clinically significant physical dependence. The risks of dependence and withdrawal increase with longer treatment duration and higher daily dose. Although Diazepam injection is indicated only for intermittent use (see INDICATIONS AND USAGE and DOSAGE AND ADMINISTRATION), if used more frequently than recommended, abrupt discontinuation or rapid dosage reduction of DIAZEPAM INJECTION may precipitate acute withdrawal reactions, which can be life-threatening. For patients using DIAZEPAM INJECTION more frequently than recommended, to reduce the risk of withdrawal reactions, use a gradual taper to discontinue DIAZEPAM INJECTION (see WARNINGS).

DESCRIPTION

Diazepam injection is a sterile solution packaged within a device that delivers its entire 2 mL contents automatically upon activation. Each mL contains 5 mg diazepam compounded with 40% propylene glycol, 10% ethyl alcohol, 5% sodium benzoate and benzoic acid as buffers, and 1.5% benzyl alcohol as preservative.

Diazepam is a benzodiazepine derivative. Chemically, diazepam is 7-chloro-1,3- dihydro- 1-methyl-5-phenyl- 2H-1, 4-benzodiazepine-2-one. It is a colorless crystalline compound, insoluble in water and has a molecular weight of 284.74. Its structural formula is as follows:

CLINICAL PHARMACOLOGY

In animals, diazepam appears to act on parts of the limbic system, the thalamus and hypothalamus, and induces calming effects. Diazepam, unlike chlorpromazine and reserpine, has no demonstrable peripheral autonomic blocking action, nor does it produce extrapyramidal side effects. However, animals treated with diazepam do have a transient ataxia at higher doses. Diazepam was found to have transient cardiovascular depressor effects in dogs. Long-term experiments in rats revealed no disturbances of endocrine function. Injections into animals have produced localized irritation of tissue surrounding injection sites and some thickening of veins after intravenous use.

Pharmacokinetics (autoinjector)

A study performed in 24 healthy male subjects comparing the I.M. Injection of 10 mg of diazepam in the mid-anterior/lateral thigh by the autoinjector versus 10 mg I.M. by a syringe (operated manually) indicates that the mean percent availability of the drug from the autoinjector is 100% of that obtained from the syringe.

In addition, the mean Cmax value from the autoinjector was 314 ng/mL (c.v. = 18.7%, range 185 to 439 ng/mL) and 48.6 ng/mL (c.v. = 19.8%, range 29.4 to 69.7 ng/mL) for diazepam and desmethyldiazepam, respectively, while the syringe gave corresponding values of 287 ng/mL (c.v. = 18.9%, range 174 to 378 ng/mL) and 47.2 ng/mL (c.v. =19.4 %, range 33.1 to 61.2 ng/mL) for diazepam and desmethyldiazepam, respectively. The corresponding mean Tmax values were 1.47 hours (c.v. = 69.9%, range 0.8 to 6 hours) and 61.0 hours (c.v. = 56.8%, range 24 to 144 hours) for diazepam and desmethyldiazepam for the autoinjector whereas the syringe gave values of 1.31 hours (c.v. =32%, range 0.7 to 2.0 hours) and 54.5 hours (c.v. = 47.3%, range 12 to 96 hours) for diazepam and desmethyldiazepam, respectively.

INDICATIONS

Diazepam is indicated for the management of anxiety disorders for the short-term relief of the symptoms of anxiety. Anxiety or tension associated with the stress of everyday life usually does not require treatment with an anxiolytic.

Note: Because the autoinjector provides a minimum dose of 10 mg diazepam, it should not be used to treat individuals with mild and moderate degrees of anxiety and anxiety related disorders that would ordinarily be managed with intramuscular doses of less than 10 mg.

In acute alcohol withdrawal, diazepam may be useful in the symptomatic relief of acute agitation, tremor, impending or acute delirium tremens and hallucinosis.

As an adjunct prior to endoscopic procedures if apprehension, anxiety or acute stress reactions are present, and to diminish the patient's recall of the procedures (See WARNINGS).

Diazepam is a useful adjunct for the relief of skeletal muscle spasm due to reflex spasm to local pathology (such as inflammation of the muscles or joints, or secondary to trauma), spasticity caused by upper motor neuron disorders (such as cerebral palsy and paraplegia); athetosis; stiff man syndrome; and tetanus.

Diazepam injection is a useful adjunct in status epilepticus and severe recurrent convulsive seizures.

Diazepam is useful premedication for relief of anxiety and tension in patients who are to undergo surgical procedures.

CONTRAINDICATIONS

INTRAVENOUS ADMINISTRATION OF DIAZEPAM WITH THE AUTOINJECTOR IS CONTRAINDICATED.

Diazepam injection is contraindicated in patients with a known hypersensitivity to this drug; acute narrow angle glaucoma; and open angle glaucoma unless patients are receiving appropriate therapy.

WARNINGS

Diazepam Autoinjector is to be administered only by the intramuscular (I.M.) route.

Risks from Concomitant Use With Opioids

Concomitant use of benzodiazepines, including diazepam, and opioids may result in profound sedation, respiratory depression, coma, and death. Because of these risks, reserve concomitant prescribing of benzodiazepines and opioids for patients for whom alternative treatment options are inadequate.

Observational studies have demonstrated that concomitant use of opioid analgesics and benzodiazepines increases the risk of drug-related mortality compared to use of opioids alone. If a decision is made to prescribe diazepam concomitantly with opioids, prescribe the lowest effective dosages and minimum durations of concomitant use, and follow patients closely for signs and symptoms of respiratory depression and sedation. Advise both patients and caregivers about the risks of respiratory depression and sedation when diazepam is used with opioids (see PRECAUTIONS).

Abuse, Misuse, and Addiction

The use of benzodiazepines, including Diazepam injection, exposes users to the risks of abuse, misuse, and addiction, which can lead to overdose or death. Abuse and misuse of benzodiazepines often (but not always) involve the use of doses greater than the maximum recommended dosage and commonly involve concomitant use of other medications, alcohol, and/or illicit substances, that is associated with an increased frequency of serious adverse outcomes, including respiratory depression, overdose, or death (see DRUG ABUSE AND DEPENDENCE: Abuse).

Before prescribing Diazepam injection and throughout treatment, assess each patient's risk for abuse, misuse, and addiction. Use of Diazepam injection, particularly in patients at elevated risk, necessitates counseling about the risks and proper use of Diazepam injection along with monitoring for signs and symptoms of abuse, misuse, and addiction. Do not exceed the recommended dosing frequency; avoid or minimize concomitant use of CNS depressants and other substances associated with abuse, misuse, and addiction (e.g., opioid analgesics, stimulants); and advise patients on the proper disposal of unused drug. If a substance use disorder is suspected, evaluate the patient and institute (or refer them for) early treatment, as appropriate.

Dependence and Withdrawal Reactions After Use of Diazepam injection More Frequently Than Recommended

For patients using Diazepam injection more frequently than recommended, to reduce the risk of withdrawal reactions, use a gradual taper to discontinue Diazepam injection (a patient-specific plan should be used to taper the dose).

Patients at an increased risk of withdrawal adverse reactions after benzodiazepine discontinuation or rapid dosage reduction include those who take higher dosages, and those who have had longer durations of use.

Acute Withdrawal Reactions

The continued use of benzodiazepines may lead to clinically significant physical dependence. Although Diazepam injection is indicated only for intermittent use (see INDICATIONS AND USAGE and DOSAGE AND ADMINISTRATION), if used more frequently than recommended, abrupt discontinuation or rapid dosage reduction of Diazepam injection, or administration of flumazenil (a benzodiazepine antagonist) may precipitate acute withdrawal reactions, which can be life-threatening (e.g., seizures) (see DRUG ABUSE AND DEPENDENCE: Dependence).

Protracted Withdrawal Syndrome

In some cases, benzodiazepine users have developed a protracted withdrawal syndrome with withdrawal symptoms lasting weeks to more than 12 months (see DRUG ABUSE AND DEPENDENCE: Dependence).

Respiratory and Central Nervous System Depression

Extreme care must be used in administering injectable diazepam to the elderly, to very ill patients and to those with limited pulmonary reserve because of the possibility that apnea and/or cardiac arrest may occur. Concomitant use of barbiturates, alcohol, or other central nervous system depressants increases depression with increased risk of apnea. Resuscitative equipment including that necessary to support respiration should be readily available.

When diazepam is used with a narcotic analgesic, the dosage of the narcotic should be reduced by at least one-third and administered in small increments. In some cases the use of a narcotic may not be necessary (see PRECAUTIONS).

Diazepam injection should not be administered to patients in shock, coma, or in acute alcoholic intoxication with depression of vital signs. As is true of most CNS-acting drugs, patients receiving diazepam should be cautioned against engaging in hazardous occupations requiring complete mental alertness, such as operating machinery or driving a motor vehicle.

Use in Patients with Petit Mal Status

Tonic status epilepticus has been precipitated in patients treated with I.V. diazepam for petit mal status or petit mal variant status.

Neonatal Sedation and Withdrawal Syndrome

Use of Diazepam injection late in pregnancy can result in sedation (respiratory depression, lethargy, hypotonia) and/or withdrawal symptoms (hyperreflexia, irritability, restlessness, tremors, inconsolable crying, and feeding difficulties) in the neonate (see PRECAUTIONS: Pregnancy). Monitor neonates exposed to Diazepam injection during pregnancy or labor for signs of sedation and monitor neonates exposed to Diazepam injection during pregnancy for signs of withdrawal; manage these neonates accordingly.

Pediatric Use

Efficacy and safety of parenteral diazepam has not been established in the neonate (30 days or less of age).

Prolonged central nervous system depression has been observed in neonates, apparently due to inability to biotransform diazepam into inactive metabolites.

PRECAUTIONS

Drug Interactions

Effect of Concomitant Use of Benzodiazepines and Opioids

The concomitant use of benzodiazepines and opioids increases the risk of respiratory depression because of actions at different receptor sites in the CNS that control respiration. Benzodiazepines interact at GABAA sites, and opioids interact primarily at mu receptors. When benzodiazepines and opioids are combined, the potential for benzodiazepines to significantly worsen opioid-related respiratory depression exists. Limit dosage and duration of concomitant use of benzodiazepines and opioids, and follow patients closely for respiratory depression and sedation.

Concomitant Use with Other Psychotropic Agents or Anticonvulsant Drugs

If diazepam is to be combined with other psychotropic agents or anticonvulsant drugs, careful consideration should be given to the pharmacology of the agents to be employed particularly with known compounds which may potentiate the action of diazepam, such as phenothiazines, narcotics, barbiturates, MAO inhibitors and other antidepressants. In highly anxious patients with evidence of accompanying depression, particularly those who may have suicidal tendencies, protective measures may be necessary. The usual precautions in treating patients with impaired hepatic function should be observed. Metabolites of diazepam are excreted by the kidney; to avoid their excess accumulation, caution should be exercised in the administration to patients with compromised kidney function.

Concomitant Use with Cimetidine

The clearance of diazepam and certain other benzodiazepines can be delayed in association with Tagamet (cimetidine) administration. The clinical significance of this is unclear.

Pregnancy

Pregnancy Exposure Registry

There is a pregnancy exposure registry that monitors pregnancy outcomes in women exposed to AEDs, such as Diazepam injection, during pregnancy. Healthcare providers are encouraged to recommend that pregnant women taking Diazepam injection enroll in the North American Antiepileptic Drug (NAAED) Pregnancy Registry by calling 1-888- 233- 2334 or online at http://www.aedpregnancyregistry.org/.

Risk Summary

Neonates born to mothers using benzodiazepines late in pregnancy have been reported to experience symptoms of sedation and/or neonatal withdrawal (see WARNINGS: Neonatal Sedation and Withdrawal Syndrome, and Clinical Considerations). Available data from published observational studies of pregnant women exposed to benzodiazepines do not report a clear association with benzodiazepines and major birth defects (see Human Data).

In animal studies, administration of diazepam during the organogenesis period of pregnancy resulted in increased incidences of fetal malformations at doses greater than those used clinically. Data for diazepam and other benzodiazepines suggest the possibility of increased neuronal cell death and long-term effects on neurobehavioral and immunological function based on findings in animals following prenatal or early postnatal exposure at clinically relevant doses (see Animal Data).

The background risk of major birth defects and miscarriage for the indicated population is unknown. All pregnancies have a background risk of birth defect, loss, or other adverse outcomes. In the U.S. general population, the estimated risk of major birth defects and of miscarriage in clinically recognized pregnancies is 2% to 4% and 15% to 20%, respectively.

Clinical Considerations

Fetal/Neonatal Adverse Reactions

Benzodiazepines cross the placenta and may produce respiratory depression, hypotonia, and sedation in neonates. Monitor neonates exposed to Diazepam injection during pregnancy or labor for signs of sedation, respiratory depression, hypotonia, and feeding problems. Monitor neonates exposed to Diazepam injection during pregnancy for signs of withdrawal. Manage these neonates accordingly (see WARNINGS: Neonatal Sedation and Withdrawal Syndrome).

Data

Human Data

Published data from observational studies on the use of benzodiazepines during pregnancy do not report a clear association with benzodiazepines and major birth defects.

Although early studies reported an increased risk of congenital malformations with diazepam and chlordiazepoxide, there was no consistent pattern noted. In addition, the majority of more recent case-control and cohort studies of benzodiazepine use during pregnancy, which were adjusted for confounding exposures to alcohol, tobacco and other medications, have not confirmed these findings.

Animal Data

Diazepam has been shown to produce increased incidences of fetal malformations in mice and hamsters when given orally at single doses of 100 mg/kg or greater (approximately 8 times the maximum recommended human dose [1 mg/kg/day] or greater on a mg/m^2 basis). Cleft palate and exencephaly are the most common and consistently reported malformations produced in these species by administration of high, maternally-toxic doses of diazepam during organogenesis.

In published animal studies, administration of benzodiazepines or other drugs that enhance GABAergic neurotransmission to neonatal rats has been reported to result in widespread apoptotic neurodegeneration in the developing brain at plasma concentration relevant for seizure control in humans. The window of vulnerability to these changes in rats (postnatal days 0-14) includes a period of brain development that takes place during the third trimester of pregnancy in humans.

Nursing Mothers

Risk Summary

Diazepam is present in breastmilk. There are reports of sedation, poor feeding and poor weight gain in infants exposed to benzodiazepines through breast milk. There are no data on the effects of diazepam on milk production. The developmental and health benefits of breastfeeding should be considered along with the mother's clinical need for Diazepam injection and any potential adverse effects on the breastfed infant from Diazepam injection or from the underlying maternal condition.

Clinical Considerations

Infants exposed to Diazepam injection through breast milk should be monitored for sedation, poor feeding and poor weight gain.

Administration Considerations

Long Term Control of Seizures

Although seizures may be brought under control promptly with a single 10 mg intramuscular dose, a significant proportion of patients may experience a return to seizure activity. Consequently, it may become necessary to re-administer the drug. The cumulative maximum dose of diazepam should not exceed 30 mg; the interval between doses should be no less than 10 minutes. Diazepam is not recommended for maintenance, and once seizures are brought under control, consideration should be given to the administration of agents useful in longer term control of seizures.

Since an increase in cough reflex and laryngospasm may occur with peroral endoscopic procedures, the use of a topical anesthetic agent and the availability of necessary countermeasures are recommended.

Hypotension and Muscular Weakness

Diazepam injection has produced hypotension or muscular weakness in some patients particularly when used with narcotics, barbiturates or alcohol.

ADVERSE REACTIONS

Side effects most commonly reported were drowsiness, fatigue and ataxia; venous thrombosis and phlebitis at the site of injection. Other adverse reactions less frequently reported include: CNS: confusion, depression, dysarthria, headache, hypoactivity, slurred speech, syncope, tremor, vertigo. G.I.: constipation, nausea. G.U.: incontinence, changes in libido, urinary retention. Cardiovascular: bradycardia, cardiovascular collapse, hypotension. EENT: blurred vision, diplopia, nystagmus. Skin: urticaria, skin rash. Other: hiccups, changes in salivation, neutropenia, jaundice. Paradoxical reactions such as acute hyperexcited states, anxiety, hallucinations, increased muscle spasticity, insomnia, rage, sleep disturbances and stimulation have been reported; should these occur, use of the drug should be discontinued.

Minor changes in EEG patterns, usually low-voltage fast activity, have been observed in patients during and after diazepam therapy and are of no known significance.

In peroral endoscopic procedures, coughing, depressed respiration, dyspnea, hyperventilation, laryngospasm and pain in throat or chest have been reported.

Because of isolated reports of neutropenia and jaundice, periodic blood counts and liver function tests are advisable during long-term therapy.

DRUG ABUSE AND DEPENDENCE

Controlled Substance

Diazepam is a schedule IV controlled substance.

Abuse

Diazepam injection is a benzodiazepine and a CNS depressant with a potential for abuse and addiction. Abuse is the intentional, non-therapeutic use of a drug, even once, for its desirable psychological or physiological effects. Misuse is the intentional use, for therapeutic purposes, of a drug by an individual in a way other than prescribed by a health care provider or for whom it was not prescribed. Drug addiction is a cluster of behavioral, cognitive, and physiological phenomena that may include a strong desire to take the drug, difficulties in controlling drug use (e.g., continuing drug use despite harmful consequences, giving a higher priority to drug use than other activities and obligations), and possible tolerance or physical dependence. Even taking benzodiazepines as prescribed may put patients at risk for abuse and misuse of their medication. Abuse and misuse of benzodiazepines may lead to addiction.

Abuse and misuse of benzodiazepines often (but not always) involve the use of doses greater than the maximum recommended dosage and commonly involve concomitant use of other medications, alcohol, and/or illicit substances, which is associated with an increased frequency of serious adverse outcomes, including respiratory depression, overdose, or death. Benzodiazepines are often sought by individuals who abuse drugs and other substances, and by individuals with addictive disorders (see WARNINGS: Abuse, Misuse, and Addiction).

The following adverse reactions have occurred with benzodiazepine abuse and/or misuse: abdominal pain, amnesia, anorexia, anxiety, aggression, ataxia, blurred vision, confusion, depression, disinhibition, disorientation, dizziness, euphoria, impaired concentration and memory, indigestion, irritability, muscle pain, slurred speech, tremors, and vertigo.

The following severe adverse reactions have occurred with benzodiazepine abuse and/or misuse: delirium, paranoia, suicidal ideation and behavior, seizures, coma, breathing difficulty, and death. Death is more often associated with polysubstance use (especially benzodiazepines with other CNS depressants such as opioids and alcohol).

Dependence

Physical Dependence After Use of Diazepam Injection More Frequently Than Recommended

Diazepam injection may produce physical dependence if used more frequently than recommended. Physical dependence is a state that develops as a result of physiological adaptation in response to repeated drug use, manifested by withdrawal signs and symptoms after abrupt discontinuation or a significant dose reduction of a drug. Although Diazepam injection is indicated only for intermittent use (see INDICATIONS AND USAGE and DOSAGE AND ADMINISTRATION), if used more frequently than recommended, abrupt discontinuation or rapid dosage reduction or administration of flumazenil, a benzodiazepine antagonist, may precipitate acute withdrawal reactions, including seizures, which can be life-threatening. Patients at an increased risk of withdrawal adverse reactions after benzodiazepine discontinuation or rapid dosage reduction include those who take higher dosages (i.e., higher and/or more frequent doses) and those who have had longer durations of use (see WARNINGS: Dependence and Withdrawal Reactions).

For patients using Diazepam injection more frequently than recommended, to reduce the risk of withdrawal reactions, use a gradual taper to discontinue Diazepam injection (see WARNINGS: Dependence and Withdrawal Reactions).

Acute withdrawal signs and symptoms associated with benzodiazepines have included abnormal involuntary movements, anxiety, blurred vision, depersonalization, depression, derealization, dizziness, fatigue, gastrointestinal adverse reactions (e.g., nausea, vomiting, diarrhea, weight loss, decreased appetite), headache, hyperacusis, hypertension, irritability, insomnia, memory impairment, muscle pain and stiffness, panic attacks, photophobia, restlessness, tachycardia, and tremor. More severe acute withdrawal signs and symptoms, including life-threatening reactions, have included catatonia, convulsions, delirium tremens, depression, hallucinations, mania, psychosis, seizures, and suicidality.

Protracted withdrawal syndrome associated with benzodiazepines is characterized by anxiety, cognitive impairment, depression, insomnia, formication, motor symptoms (e.g., weakness, tremor, muscle twitches), paresthesia, and tinnitus that persists beyond 4 to 6 weeks after initial benzodiazepine withdrawal. Protracted withdrawal symptoms may last weeks to more than 12 months. As a result, there may be difficulty in differentiating withdrawal symptoms from potential re-emergence or continuation of symptoms for which the benzodiazepine was being used.

Tolerance

Tolerance to Diazepam injection may develop after use more frequently than recommended. Tolerance is a physiological state characterized by a reduced response to a drug after repeated administration (i.e., a higher dose of a drug is required to produce the same effect that was once obtained at a lower dose). Tolerance to the therapeutic effect of benzodiazepines may develop; however, little tolerance develops to the amnestic reactions and other cognitive impairments caused by benzodiazepines.

OVERDOSAGE

Overdosage of benzodiazepines is characterized by central nervous system depression ranging from drowsiness to coma. In mild to moderate cases, symptoms can include drowsiness, confusion, dysarthria, lethargy, hypnotic state, diminished reflexes, ataxia, and hypotonia. Rarely, paradoxical or disinhibitory reactions (including agitation, irritability, impulsivity, violent behavior, confusion, restlessness, excitement, and talkativeness) may occur. In severe overdosage cases, patients may develop respiratory depression and coma. Overdosage of benzodiazepines in combination with other CNS depressants (including alcohol and opioids) may be fatal (see Warnings: Abuse, Misuse, and Addiction). Markedly abnormal (lowered or elevated) blood pressure, heart rate, or respiratory rate raise the concern that additional drugs and/or alcohol are involved in the overdosage.

In managing benzodiazepine overdosage, employ general supportive measures, including intravenous fluids and airway maintenance. Flumazenil, a specific benzodiazepine receptor antagonist indicated for the complete or partial reversal of the sedative effects of benzodiazepines in the management of benzodiazepine overdosage, can lead to withdrawal and adverse reactions, including seizures, particularly in the context of mixed overdosage with drugs that increase seizure risk (e.g., tricyclic and tetracyclic antidepressants) and in patients with long-term benzodiazepine use and physical dependency. The risk of withdrawal seizures with flumazenil use may be increased in patients with epilepsy. Flumazenil is contraindicated in patients who have received a benzodiazepine for control of a potentially life-threatening condition (e.g., status epilepticus). If the decision is made to use flumazenil, it should be used as an adjunct to, not as a substitute for, supportive management of benzodiazepine overdosage. See the flumazenil injection Prescribing Information.

Consider contacting the Poison Help line (1-800-221-2222) or a medical toxicologist for additional overdosage management recommendations.

DOSAGE AND ADMINISTRATION (INTRAMUSCULAR ONLY)

Administration of the Diazepam Autoinjector

1. Pull off gray safety cap
2. Place Black end on mid outer thigh
3. Push hard until injector functions
4. Withdraw after 10 seconds

Dosage

Caution: Because the autoinjector automatically delivers a fixed dose of 10 mg of diazepam, it cannot be used in situations requiring lower total doses or those in which small incremental increases of diazepam are required.

The usual recommended dose in older children and adults ranges from 10 mg to 20 mg I.M. depending on the indication and its severity. The cumulative total dose and individual maximum dose for intramuscular administration will vary with the specific indication (See dosage for specific indications).

Intramuscular

When instructions are followed properly the Diazepam Autoinjector injects deeply into the muscle.

Intravenous Use

The Diazepam Autoinjector is not designed or intended for intravenous use.

Severe Anxiety Disorders and Symptoms of Anxiety

Usual Adult Dosage: 10 mg, I. M. Repeat in 3 to 4 hours, if necessary.

Acute Alcohol Withdrawal

As an aid in symptomatic relief of acute agitation, tremor, impending or acute delirium tremens and hallucinosis.

Usual Adult Dosage: 10 mg, I. M. initially, then 10 mg in 3 to 4 hours, if necessary.

Endoscopic procedures

Adjunctively, if apprehension, anxiety or acute stress reactions are present prior to endoscopic procedures. Dosage of narcotics should be reduced by at least a third and in some cases may be omitted. See Precautions for peroral procedures.

Usual Adult Dosage: 10 mg I. M., approximately 30 minutes prior to the procedure.

Muscle Spasm

Associated with local pathology, cerebral palsy, athetosis, stiff-man syndrome or tetanus.

Usual Adult Dosage: 10 mg, I. M., initially, then 10 mg in 3 to 4 hours, if necessary. For tetanus, larger doses may be required.

Status Epilepticus and Severe Recurrent Convulsive Seizures

In the convulsing patient, the I.V. route is preferred. However, if conditions preclude intravenous administration, the I.M. route may be used.

Usual Adult Dosage: 10 mg, initially. This injection may be repeated if necessary at 10 to 15 minute intervals up to a maximum dose of 30 mg. If necessary, therapy with diazepam may be repeated in 2 to 4 hours; however, residual active metabolites may persist, and re-administration should be made with this consideration.

Extreme caution must be exercised with individuals with chronic lung disease or unstable cardiovascular status.

Preoperative Medication

To relieve anxiety and tension. (if atropine, scopolamine or other premedications are desired, they must be administered in separate syringes).

Usual Adult Dosage: 10 mg, I.M. (preferred route), before surgery.

General

Once the acute symptomatology has been properly controlled with diazepam injection, the patient may be placed on oral therapy with diazepam if further treatment is required. Parenteral drug products should be inspected visually for particulate matter and discoloration prior to administration, whenever the solution and container permit.

HOW SUPPLIED

Diazepam injection, 5 mg per mL, is available in 2 mL Disposable Autoinjectors.

STORAGE

Store at 25°C (77°F); Excursions permitted to 15-30°C (59-86°F). [See USP Controlled Room Temperature]. Do not refrigerate.

Office of the Surgeon General
U.S. Army Medical Research and Development Command (MCMR-RCQ-HR) Fort Detrick
Frederick, Maryland 21702-5012

Manufactured by:
Meridian Medical Technologies,
LLC

Revision: 1/2023

0001966

PRINCIPAL DISPLAY PANEL - 10 mg Autoinjector Label

Meridian™
MEDICAL TECHNOLOGIES
St. Louis, MO 63146

AUTOINJECTOR
FOR BUDDY USE

Store at 25°C (77°F); Excursions permitted
to 15 - 30°C (59 - 86°F). [See USP Controlled
Room Temperature]. Do not refrigerate.

AUTOINJECTOR
FOR BUDDY USE

Rx Only

1. Pull off gray safety cap

2. Place black end on mid outer thigh and

3. Push hard until injector functions

4. Withdraw after 10 seconds

Meridian™
MEDICAL TECHNOLOGIES

0002201

NSN 6505-01-274-0951 C-IV

DIAZEPAM INJECTION, USP, 10 mg AUTOMATIC